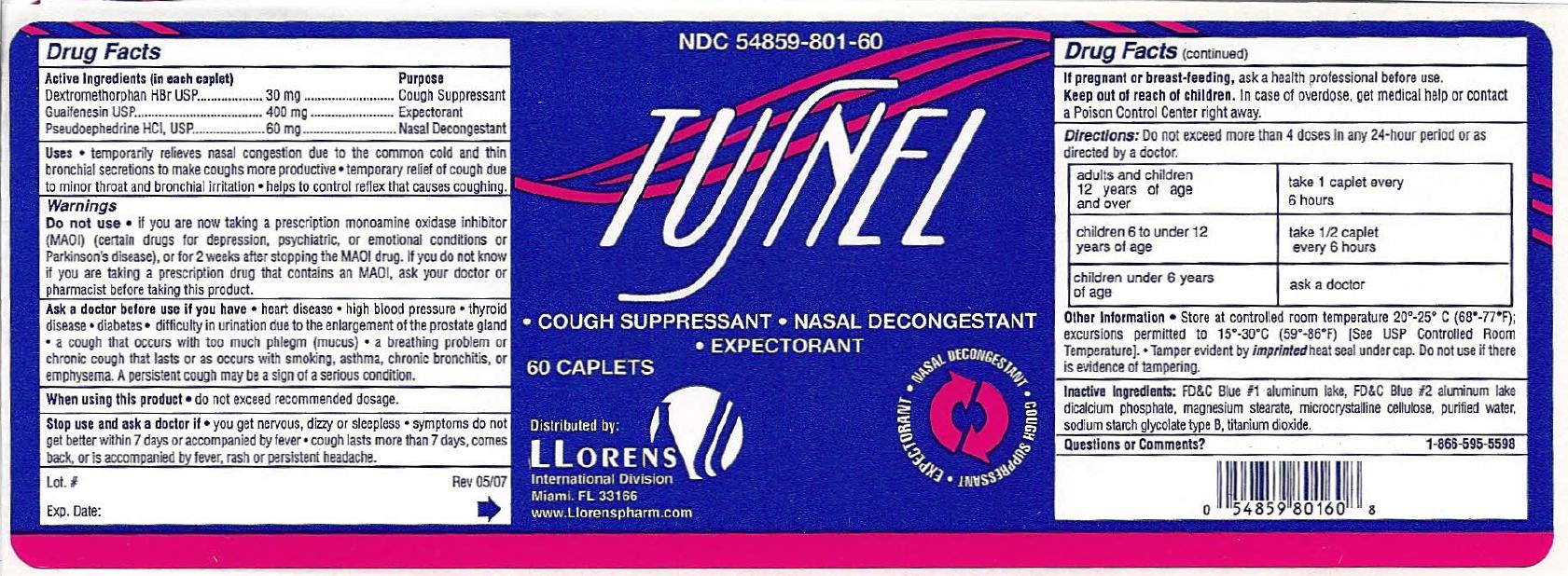 DRUG LABEL: Tusnel
NDC: 54859-801 | Form: TABLET
Manufacturer: LLORENS PHARMACEUTICALS INTERNATIONAL DIVISION
Category: otc | Type: HUMAN OTC DRUG LABEL
Date: 20201223

ACTIVE INGREDIENTS: DEXTROMETHORPHAN HYDROBROMIDE 30 mg/1 1; GUAIFENESIN 400 mg/1 1; PSEUDOEPHEDRINE HYDROCHLORIDE 60 mg/1 1
INACTIVE INGREDIENTS: FD&C BLUE NO. 2; FD&C BLUE NO. 1; ANHYDROUS DIBASIC CALCIUM PHOSPHATE; MAGNESIUM STEARATE; CELLULOSE, MICROCRYSTALLINE; WATER; SODIUM STARCH GLYCOLATE TYPE B POTATO; TITANIUM DIOXIDE

DRUG FACTS

Active Ingredients (In each tablet) Purpose

Dextromethorphan HBr ................... 30 mg ................... Cough Suppressant

Guaifenesin .................................. 400 mg .................. Expectorant

Pseudoephedrine HCl .................... 60 mg .................... Nasal Decongestant

Uses

- temporarily relieves nasal congestion due to the common cold and thin bronchial secretions to make coughs more productive
- temporary relief of cough due to minor throat and bronchial irritation
- helps to control reflex that causes coughing

Warnings

Ask a doctor before use if you have

- heart disease
- high blood pressure
- thyroid disease
- diabetes
- difficulty in urination due to the enlargement of the prostate gland
- a cough that occurs with too much phlegm (mucus)
- a breathing problem or chronic cough that lasts or as occurs with smoking, asthma, chronic bronchitis, or emphysema. A persistent cough may be a sign of a serious condition.

When using this product do not exceed recommended dosage.

Stop use and ask a doctor if

- you get nervous, dizzy or sleepless
- symptoms do not get better within 7 days or accompanied by fever
- cough lasts more than 7 days, comes back or is accompanied by fever, rash or persistent headache

Do not use

- if you are now taking a prescription monamine oxidase inhibitor (MAOI) (certain drugs for depression, psychiatric, or emotional conditions or Parkinson's disease), or for 2 weeks after stopping the MAOI drug. If you do not know if you are taking a prescription drug that contains on MAOI, ask your doctor or pharmacist before taking this product.

Keep out of reach of children.In case of overdose, get medical help or contact a Poison Control Center right away

PREGNANCY OR BREAST FEEDING

If pregnant or breast-feeding,ask a health professional before use.

DOSAGE AND ADMINISTRATION

Directions:Do not exceed more than 4 doses in any 24-hour period or as directed by a doctor.

adults and children 12 years of age and over | take 1 tablet every 6 hours
children 6 to under 12 years of age | take 1/2 tablet every 6 hours
children under 6 years of age | ask a doctor

Other Information

Store at controlled room temperature 20-25 degrees C (68-77 degrees F); excursions permitted to 15-30 degrees C (59-86 degrees F)

Tamper evident by imprinted heat seal under cap. Do not use if there is evidence of tampering

INACTIVE INGREDIENT

Inactive Ingredients: FD and C Blue No. 1, FD and C Blue No. 2, dicalcium phosphate, magnesium stearate, microcrystalline cellulose, purified water, sodium starch glycolate type B, titanium dioxide.

Questions or Comments? 1-866-595-5598